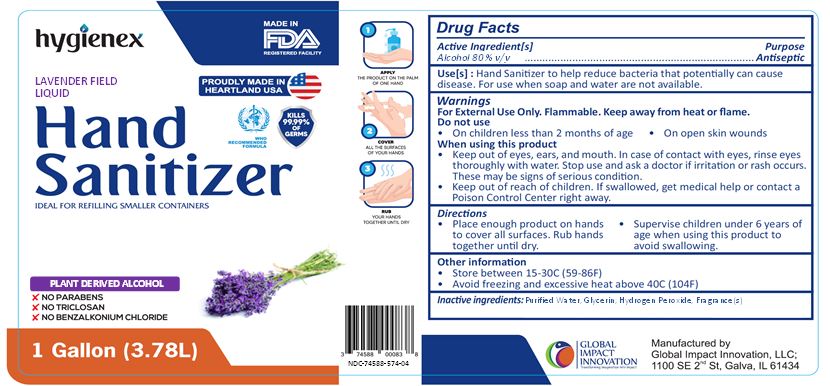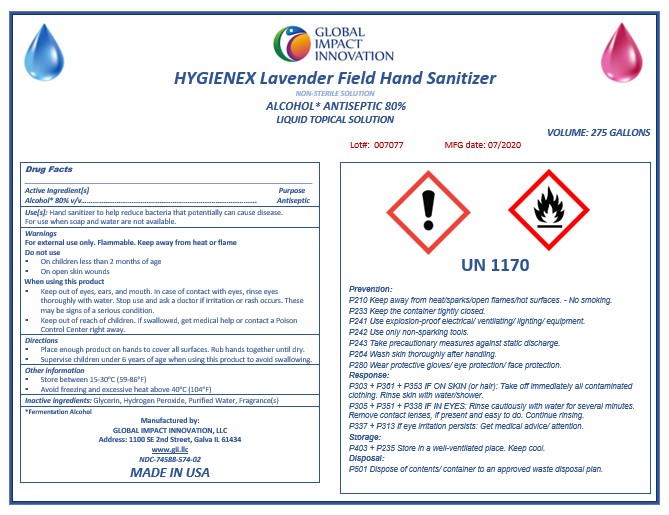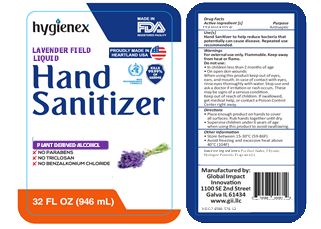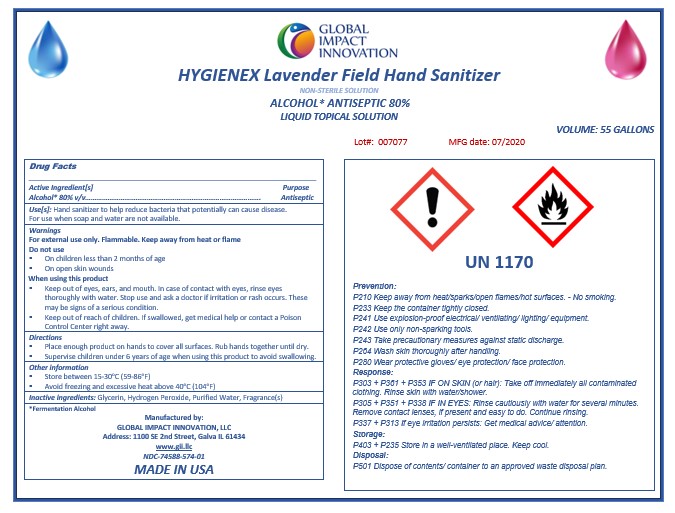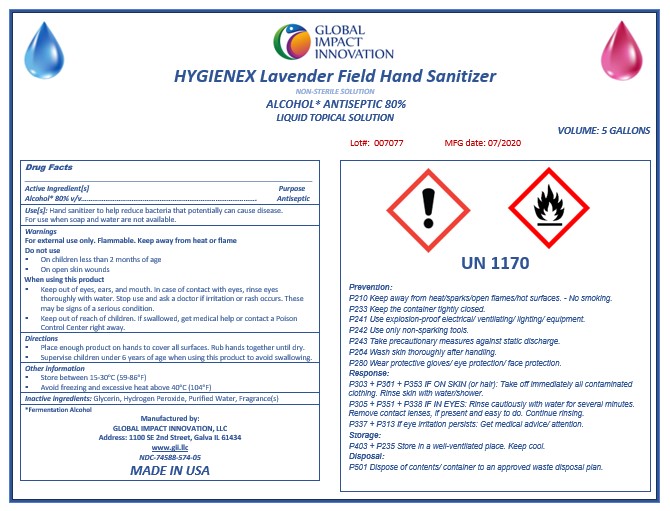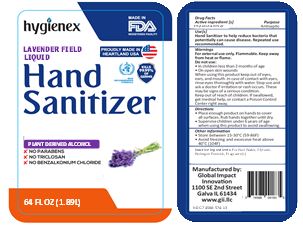 DRUG LABEL: Hygienex Lavender Field Hand Sanitizer
NDC: 74588-574 | Form: LIQUID
Manufacturer: Global Impact Innovation LLC
Category: otc | Type: HUMAN OTC DRUG LABEL
Date: 20200811

ACTIVE INGREDIENTS: ALCOHOL 80 mL/100 mL
INACTIVE INGREDIENTS: GLYCERIN; HYDROGEN PEROXIDE; WATER

Active Ingredient(s)

Alcohol 80% v/v. Purpose: Antiseptic

Purpose

Antiseptic, Hand Sanitizer

Use

Hand Sanitizer to help reduce bacteria that potentially can cause disease. For use when soap and water are not available.

Warnings

For external use only. Flammable. Keep away from heat or flame

Do not use

- in children less than 2 months of age
- on open skin wounds

When using this product keep out of eyes, ears, and mouth. In case of contact with eyes, rinse eyes thoroughly with water.
Stop use and ask a doctor if irritation or rash occurs. These may be signs of a serious condition.
Keep out of reach of children. If swallowed, get medical help or contact a Poison Control Center right away.

Stop use and ask a doctor if irritation or rash occurs. These may be signs of a serious condition.

Keep out of reach of children. If swallowed, get medical help or contact a Poison Control Center right away.

Directions

- Place enough product on hands to cover all surfaces. Rub hands together until dry.
- Supervise children under 6 years of age when using this product to avoid swallowing.

Other information

- Store between 15-30C (59-86F)
- Avoid freezing and excessive heat above 40C (104F)

Inactive ingredients

glycerin, hydrogen peroxide, purified water, fragrance(s)

Package Label - Principal Display Panel

5 Gallons NDC: 74588-574-05

55 Gallons NDC: 74588-574-01

275 Gallons NDC: 74588-574-02

1 Gallons NDC: 74588-574-04

32 Oz NDC: 74588-574-12

64 Oz NDC: 74588-574-13